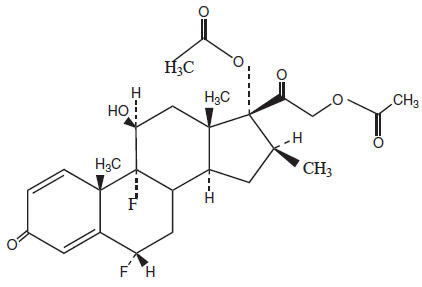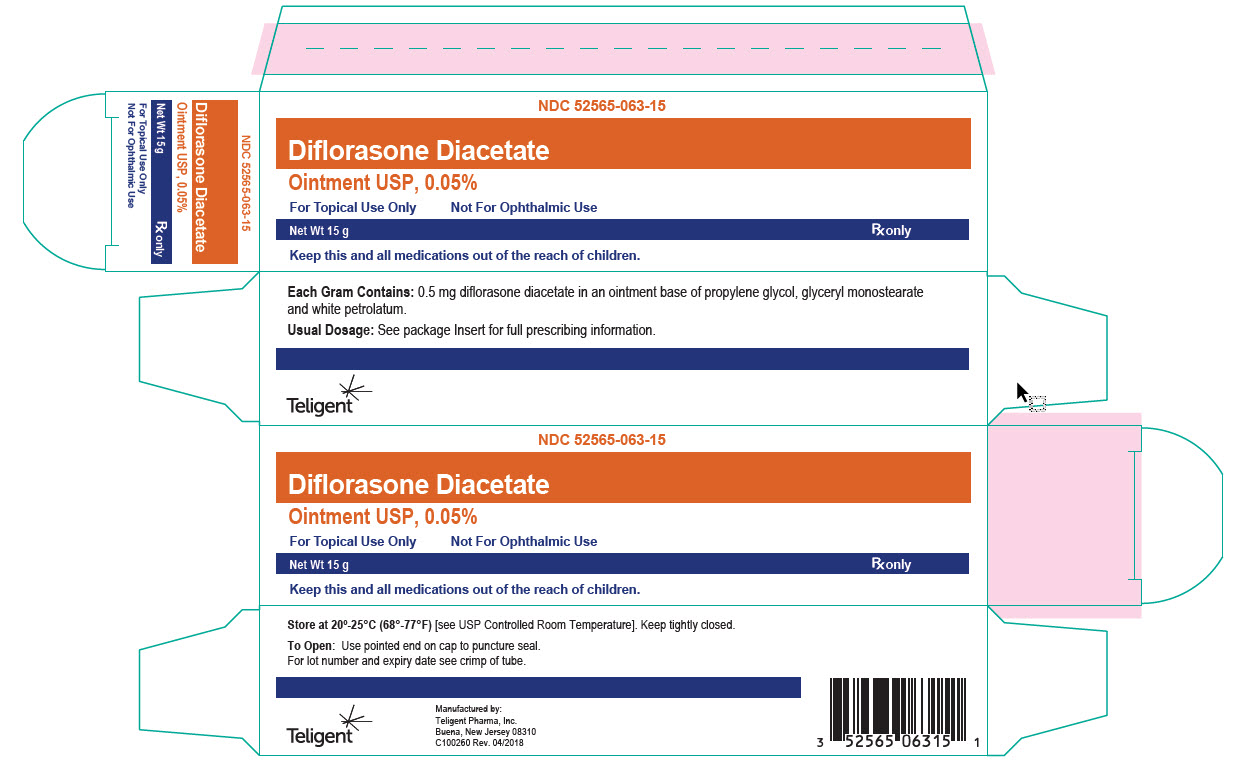 DRUG LABEL: Diflorasone Diacetate
NDC: 52565-063 | Form: OINTMENT
Manufacturer: Teligent Pharma, Inc.
Category: prescription | Type: HUMAN PRESCRIPTION DRUG LABEL
Date: 20180613

ACTIVE INGREDIENTS: Diflorasone Diacetate 0.5 mg/1 g
INACTIVE INGREDIENTS: propylene glycol; glyceryl monostearate; petrolatum

Diflorasone Diacetate
Ointment USP, 0.05%

Rx only

For Topical Use Only - Not for Ophthalmic Use.

DESCRIPTION

Each gram of diflorasone diacetate ointment contains 0.5 mg diflorasone diacetate in an ointment base.

Chemically, diflorasone diacetate is 6α,9-difluoro-11β,17,21-trihydroxy-16β-methylpregna-1,4-diene-3,20-dione 17,21-diacetate. The structural formula is represented below:

molecular formula:
C26H32F2O7
molecular weight:
494.54

Each gram of diflorasone diacetate ointment contains 0.5 mg diflorasone diacetate in an ointment base of glyceryl monostearate, propylene glycol and white petrolatum.

CLINICAL PHARMACOLOGY

Topical corticosteroids share anti-inflammatory, antipruritic and vasoconstrictive actions.

MECHANISM OF ACTION

The mechanism of anti-inflammatory activity of the topical corticosteroids is unclear. Various laboratory methods, including vasoconstrictor assays, are used to compare and predict potencies and/or clinical efficacies of the topical corticosteroids. There is some evidence to suggest that a recognizable correlation exists between vasoconstrictor potency and therapeutic efficacy in man.

Pharmacokinetics

The extent of percutaneous absorption of topical corticosteroids is determined by many factors including the vehicle, the integrity of the epidermal barrier, and the use of occlusive dressings.

Topical corticosteroids can be absorbed from normal intact skin. Inflammation and/or other disease processes in the skin increase percutaneous absorption. Occlusive dressings substantially increase the percutaneous absorption of topical corticosteroids. Thus, occlusive dressings may be a valuable therapeutic adjunct for treatment of resistant dermatoses. (See DOSAGE AND ADMINISTRATION.)

Once absorbed through the skin, topical corticosteroids are handled through pharmacokinetic pathways similar to systemically administered corticosteroids. Corticosteroids are bound to plasma proteins in varying degrees. They are metabolized primarily in the liver and are then excreted by the kidneys. Some of the topical corticosteroids and their metabolites are also excreted into the bile.

INDICATIONS AND USAGE

Topical corticosteroids are indicated for relief of the inflammatory and pruritic manifestations of corticosteroid-responsive dermatoses.

CONTRAINDICATIONS

Topical steroids are contraindicated in those patients with a history of hypersensitivity to any of the components of the preparation.

WARNINGS

Use of topical corticosteroids, including diflorasone diactate dintment may increase the risk of posterior subcapsular cataracts and glaucoma. Cataracts have been reported in postmarketing experience with the use of topical diflorasone diacetate products. Glaucoma, with possible damage to the optic nerve, and increased intraocular pressure have been reported in postmarketing experience with the use of topical dermal corticosteroids.

Avoid contact of Diflorasone Diacetate Ointment with eyes. Advise patients to report any visual symptoms.

PRECAUTIONS

General

Systemic absorption of topical corticosteroids has produced reversible hypothalamic-pituitary-adrenal (HPA) axis suppression, manifestations of Cushing's syndrome, hyperglycemia, and glucosuria in some patients.

Conditions which augment systemic absorption include the application of the more potent steroids, use over large surface areas, prolonged use, and the addition of occlusive dressings.

Therefore, patients receiving a large dose of a potent topical steroid applied to a large surface area or under an occlusive dressing should be evaluated periodically for evidence of HPA axis suppression by using the urinary free cortisol and ACTH stimulation tests. If HPA axis suppression is noted, an attempt should be made to withdraw the drug, to reduce the frequency of application, or to substitute a less potent steroid.

Recovery of HPA axis function is generally prompt and complete upon discontinuation of the drug. Infrequently, signs and symptoms of steroid withdrawal may occur, requiring supplemental systemic corticosteroids.

Pediatric patients may absorb proportionally larger amounts of topical corticosteroids and thus be more susceptible to systemic toxicity. (See PRECAUTIONS - Pediatric Use.)

If irritation develops, topical corticosteroids should be discontinued and appropriate therapy instituted.

In the presence of dermatological infections, the use of an appropriate antifungal or antibacterial agent should be instituted. If a favorable response does not occur promptly, the corticosteroid should be discontinued until the infection has been adequately controlled.

Information for the Patient

Patients using topical corticosteroids should receive the following information and instructions:

1. This medication is to be used as directed by the physician. It is for external use only. Avoid contact with the eyes.
2. Patients should be advised not to use this medication for any disorder other than for which it was prescribed.
3. Contact your healthcare provider if you experience blurred vision or other visual disturbances (see WARNINGS).
4. The treated skin area should not be bandaged or otherwise covered or wrapped as to be occlusive unless directed by the physician.
5. Patients should report any signs of local adverse reactions especially under occlusive dressing.
6. Parents of pediatric patients should be advised not to use tight-fitting diapers or plastic pants on an infant or child being treated in the diaper area, as these garments may constitute occlusive dressings.

Laboratory Tests

The following tests may be helpful in evaluating the HPA axis suppression:

Urinary free cortisol test
ACTH stimulation test

Carcinogenesis, Mutagenesis, Impairment of Fertility

Long-term animal studies have not been performed to evaluate the carcinogenic potential or the effect on fertility of topical corticosteroids.

Diflorasone diacetate was not mutagenic in a micronucleus test in rats at intraperitoneal doses up to 2400 mg/kg.

Pregnancy

Corticosteroids are generally teratogenic in laboratory animals when administered systemically at relatively low dosage levels. The more potent corticosteroids have been shown to be teratogenic after dermal application in laboratory animals. There are no adequate and well-controlled studies in pregnant women on teratogenic effects from topically applied corticosteroids. Therefore, topical corticosteroids should be used during pregnancy only if the potential benefit justifies the potential risk to the fetus. Drugs of this class should not be used extensively on pregnant patients, in large amounts, or for prolonged periods of time.

Nursing Mothers

It is not known whether topical administration of corticosteroids could result in sufficient systemic absorption to produce detectable quantities in breast milk. Because many drugs are excreted in human milk, caution should be exercised when Diflorasone Diacetate Ointment is administered to a nursing woman.

Pediatric Use

Safety and effectiveness of diflorasone diacetate ointment in pediatric patients have not been established. Because of a higher ratio of skin surface area to body mass, pediatric patients are at a greater risk than adults of HPA axis suppression when they are treated with topical corticosteroids. They are, therefore, also at greater risk of glucocorticosteroid insufficiency after withdrawal of treatment and of Cushing's syndrome while on treatment. Adverse effects including striae have been reported with inappropriate use of topical corticosteroids in pediatric patients.

HPA axis suppression, Cushing's syndrome, and intracranial hypertension have been reported in pediatric patients receiving topical corticosteroids. Manifestations of adrenal suppression in pediatric patients include linear growth retardation, delayed weight gain, low plasma cortisol levels, and absence of response to ACTH stimulation. Manifestations of intracranial hypertension include bulging fontanelles, headaches, and bilateral papilledema.

Geriatric Use

Clinical studies of diflorasone diacetate topical formulations did not include sufficient numbers of subjects aged 65 and over to determine whether they respond differently from younger subjects.

ADVERSE REACTIONS

The following local adverse reactions have been identified from clinical trials or postmarketing surveillance. Because they are reported from a population from unknown size, it is not always possible to reliably estimate their frequency or establish a causal relationship to topical corticosteroids exposure.
These adverse reactions may occur more frequently with the use of occlusive dressings or prolonged use of topical corticosteroids.

Skin and Subcutaneous Tissue Disorders: burning, itching, irritation, dryness, folliculitis, hypertrichosis, acneiform eruptions, hypopigmentation, perioral dermatitis, allergic contact dermatitis, maceration of the skin, secondary infection, skin atrophy, striae, and miliaria.

Vision Disorders: cataract, glaucoma, central serous chorioretinopathy

To report SUSPECTED ADVERSE REACTIONS, contact Teligent Pharma, Inc. at 1-856-697-1441, or FDA at 1-800-FDA-1088 or www.fda.gov/medwatch.

OVERDOSAGE

Topically applied corticosteroids can be absorbed in sufficient amounts to produce systemic effects. (See PRECAUTIONS.)

DOSAGE AND ADMINISTRATION

Diflorasone diacetate ointment should be applied to the affected area as a thin film from one to three times daily depending on the severity or resistant nature of the condition.

For topical us only. Avoid contact with eyes.
Wash hands after each application.
Do not use with occlusive dressings, unless directed by a physician (see PRECAUTIONS).
If an infection develops, the use of occlusive dressings should be discontinued and appropriate antimicrobial therapy initiated.

HOW SUPPLIED

Diflorasone Diacetate Ointment USP, 0.05% is available in 15 gram (NDC52565-063-15), 30 gram (NDC 52565-063-30) and 60 gram (NDC 52565-063-60) tubes.

STORAGE AND HANDLING

Store at 20° to 25°C (68° to 77°F) [see USP Controlled Room Temperature].

Manufactured by:
Teligent Pharma, Inc.
Buena, NJ 08310

Revised: 04/2018

PRINCIPAL DISPLAY PANEL - 15 g Tube Carton

NDC 52565-063-15

Diflorasone Diacetate
Ointment USP, 0.05%

For Topical Use Only
Not For Ophthalmic Use

Net Wt. 15 g Rx only

Keep this and all medications out of the reach of children.

Teligent Pharma, Inc.